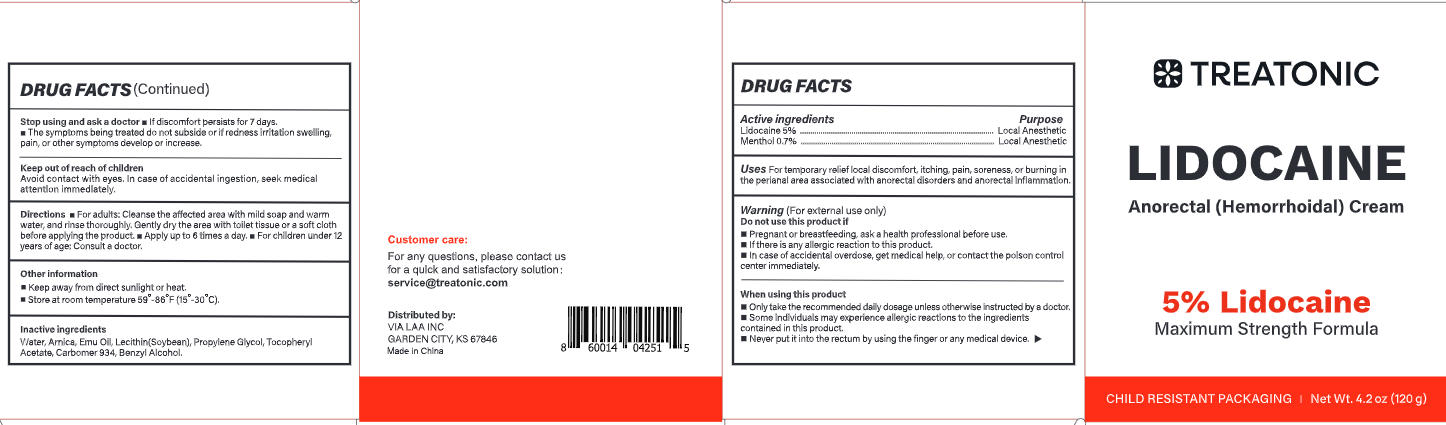 DRUG LABEL: Lidocaine numbing cream
NDC: 85569-011 | Form: CREAM
Manufacturer: 100 KARMA INC
Category: otc | Type: HUMAN OTC DRUG LABEL
Date: 20251230

ACTIVE INGREDIENTS: MENTHOL 0.84 g/120 g; LIDOCAINE 6 g/120 g
INACTIVE INGREDIENTS: WATER; EMU OIL; LECITHIN, SOYBEAN; ARNICA MONTANA; PROPYLENE GLYCOL; BENZYL ALCOHOL; CARBOMER 934; .ALPHA.-TOCOPHEROL ACETATE

Initial Drug Listing - Treatonic Lidocaine numbing cream

ACTIVE INGREDIENT

Lidocaine 5%

Menthol 0.7%

PURPOSE

Local Anesthetic

DOSAGE AND ADMINISTRATION

For temporary relief local discomfort, itching, pain, soreness, or burning in the perianal area associated with anorectal disorders and anorectal inflammation.

WARNINGS

For external use only

Do not use this product if

- Pregnant or breastfeeding, ask a health professional before use.
- lf there is any allergic reaction to this product.
- In case of accidental overdose, get medical help, or contact the poison control center immediately.

WHEN USING

- Only take the recommended daily dosage unless otherwise instructed by a doctor.
- Some individuals may experience allergic reactions to the ingredients contained in this product.
- Never put it into the rectum by using the finger or any medical device.

Stop using and ask a doctor

- If discomfort persists for 7 days.
- The symptoms being treated do not subside or if redness irritation swelling,pain,or other symptoms develop or increase.

KEEP OUT OF REACH OF CHILDREN

Avoid contact with eyes.In case of accidental ingestion, seek medical attention immediately.

INDICATIONS AND USAGE

- For adults: Cleanse the affected area with mild soap and warmwater, and rinse thoroughly, Gently dry the area with toilet tissue or a soft cloth before applying the product,
- Apply up to 6 times a day,
- For children under 12 years of age: Consult a doctor.

OTHER SAFETY INFORMATION

- Keep away from direct sunlight or heat.
- Store at room temperature 59°-86°F (15°-30°C)

INACTIVE INGREDIENT

Water, Arnica, Emu Oil, Lecithin(Soybean), Propylene Glycol, Tocopheryl Acetate, Carbomer 934, Benzyl Alcohol.